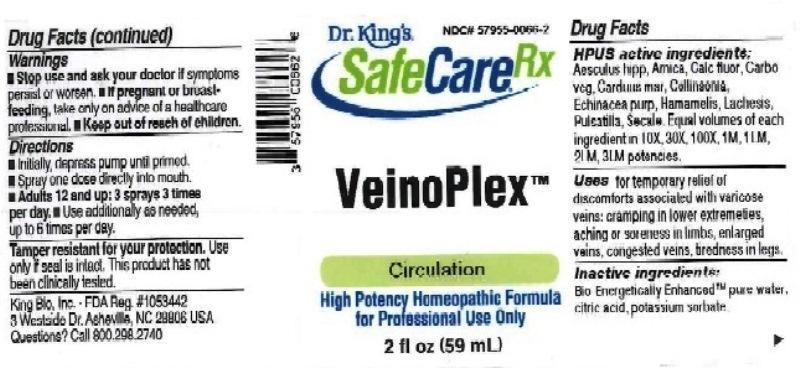 DRUG LABEL: VeinoPlex
NDC: 57955-0066 | Form: LIQUID
Manufacturer: King Bio Inc.
Category: homeopathic | Type: HUMAN OTC DRUG LABEL
Date: 20161122

ACTIVE INGREDIENTS: HORSE CHESTNUT 10 [hp_X]/59 mL; ARNICA MONTANA 10 [hp_X]/59 mL; CALCIUM FLUORIDE 10 [hp_X]/59 mL; ACTIVATED CHARCOAL 10 [hp_X]/59 mL; MILK THISTLE 10 [hp_X]/59 mL; COLLINSONIA CANADENSIS ROOT 10 [hp_X]/59 mL; ECHINACEA PURPUREA 10 [hp_X]/59 mL; HAMAMELIS VIRGINIANA ROOT BARK/STEM BARK 10 [hp_X]/59 mL; LACHESIS MUTA VENOM 10 [hp_X]/59 mL; PULSATILLA VULGARIS 10 [hp_X]/59 mL; CLAVICEPS PURPUREA SCLEROTIUM 10 [hp_X]/59 mL
INACTIVE INGREDIENTS: WATER; ANHYDROUS CITRIC ACID; POTASSIUM SORBATE

VeinoPlex

ACTIVE INGREDIENT

Drug Facts__________________________________________________________________________________________________________

HPUS active ingredients: Aesculus hippocastanum, Arnica montana, Calcarea fluorica, Carbo vegetabilis, Carduus marianus, Collinsonia canadensis, Echinacea purpurea, Hamamelis virginiana, Lachesis mutus, Pulsatilla, Secale cornutum. Equal volumes of each ingredient in 10X, 30X, 100X, 1M, 1LM, 2LM, 3LM potencies.

INDICATIONS AND USAGE

Uses for temporary relief of discomforts associated with varicose veins: cramping in lower extremities, aching or soreness in limbs, enlarged veins, congested veins, tiredness in legs.

Inactive Ingredients:

Bio-Energetically Enhanced™ pure water, citric acid and potassium sorbate.

Warnings

- Stop use and ask your doctor if symptoms persist or worsen.
- If pregnant or breast-feeding, take only on advice of a healthcare professional.

- Keep out of reach of children.

Directions

- Initially, depress pump until primed.
- Spray one dose directly into mouth.
- Adults 12 and up: 3 sprays 3 times per day
- Use additionally as needed, up to 6 times per day.

OTHER SAFETY INFORMATION

Tamper resistant for your protection. Use only if safety seal is intact. This product has not been clinically tested.

PURPOSE

Uses for temporary relief of discomforts associated with varicose veins:

- cramping in lower extremities
- aching or soreness in limbs
- enlarged veins
- congested veins
- tiredness in legs